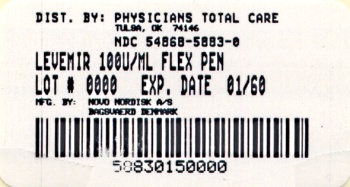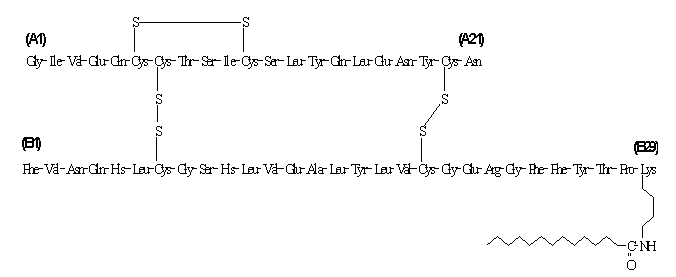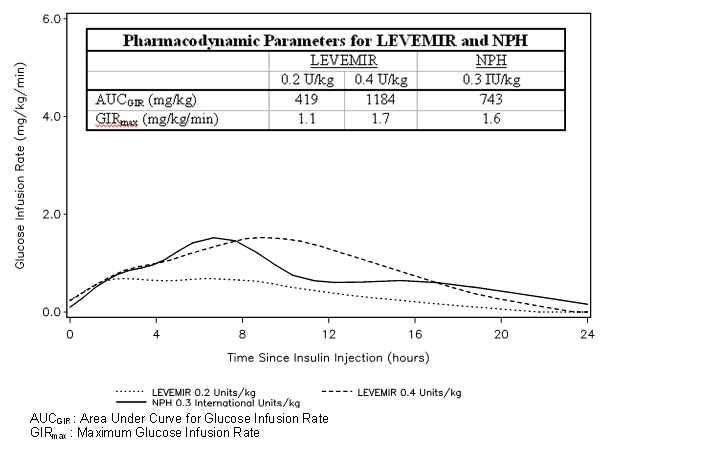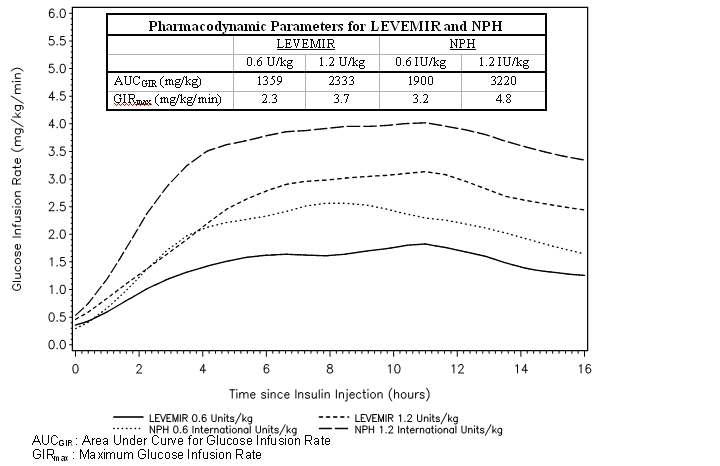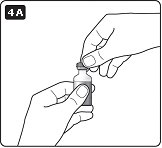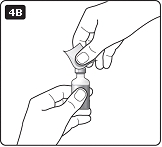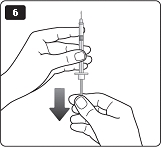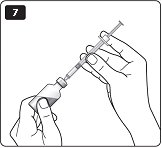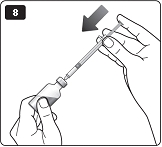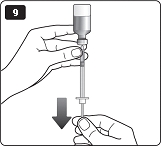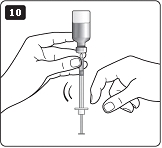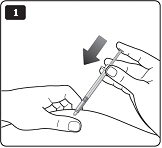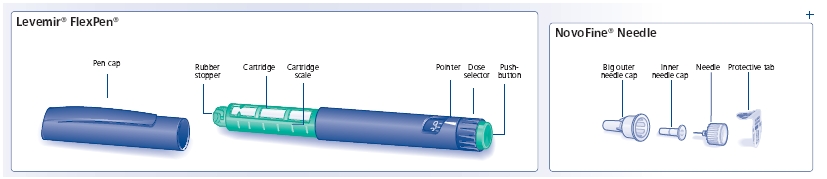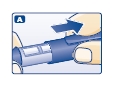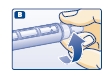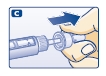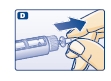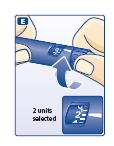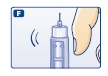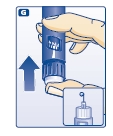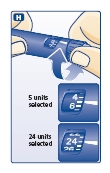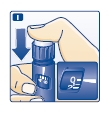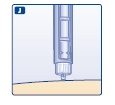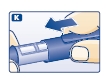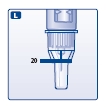 DRUG LABEL: Levemir
NDC: 54868-5883 | Form: INJECTION, SOLUTION
Manufacturer: Physicians Total Care, Inc.
Category: prescription | Type: HUMAN PRESCRIPTION DRUG LABEL
Date: 20120302

ACTIVE INGREDIENTS: INSULIN DETEMIR 14.2 mg/1 mL
INACTIVE INGREDIENTS: GLYCERIN 16.0 mg/1 mL; HYDROCHLORIC ACID; METACRESOL 2.06 mg/1 mL; PHENOL 1.80 mg/1 mL; SODIUM CHLORIDE 1.17 mg/1 mL; SODIUM HYDROXIDE; SODIUM PHOSPHATE, DIBASIC, DIHYDRATE 0.89 mg/1 mL; ZINC 65.4 ug/1 mL

HIGHLIGHTS OF PRESCRIBING INFORMATION

These highlights do not include all the information needed to use LEVEMIR® safely and effectively.
See full prescribing information for LEVEMIR.
LEVEMIR® (insulin detemir [rDNA origin] injection) solution for subcutaneous injection
Initial U.S. Approval: 2005

1 INDICATIONS AND USAGE

LEVEMIR is a long-acting human insulin analog indicated to improve glycemic control in adults and children with diabetes mellitus. (1)

Important Limitations of Use:

- Not recommended for treating diabetic ketoacidosis. Use intravenous, rapid-acting or short-acting insulin instead.

2 DOSAGE AND ADMINISTRATION

- The starting dose should be individualized based on the type of diabetes and whether the patient is insulin-naïve (2.1, 2.2, 2.3)
- Administer subcutaneously once daily or in divided doses twice daily. Once daily administration should be given with the evening meal or at bedtime (2.1)
- Rotate injection sites within an injection area (abdomen, thigh, or deltoid) to reduce the risk of lipodystrophy (2.1)
- Converting from other insulin therapies may require adjustment of timing and dose of LEVEMIR. Closely monitor glucoses especially upon converting to LEVEMIR and during the initial weeks thereafter (2.3)

3 DOSAGE FORMS AND STRENGTHS

Solution for injection 100 Units/mL (U-100) in

- 3 mL LEVEMIR FlexPen®
- 10 mL vial (3)

4 CONTRAINDICATIONS

- Do not use in patients with hypersensitivity to LEVEMIR or any of its excipients (4)

5 WARNINGS AND PRECAUTIONS

- Dose adjustment and monitoring: Monitor blood glucose in all patients treated with insulin. Insulin regimens should be modified cautiously and only under medical supervision (5.1)
- Administration: Do not dilute or mix with any other insulin or solution. Do not administer subcutaneously via an insulin pump, intramuscularly, or intravenously because severe hypoglycemia can occur (5.2)
- Hypoglycemia is the most common adverse reaction of insulin therapy and may be life-threatening (5.3, 6.1)
- Allergic reactions: Severe, life-threatening, generalized allergy, including anaphylaxis, can occur. (5.4)
- Renal or hepatic impairment: May require adjustment of the LEVEMIR dose (5.5, 5.6).

6 ADVERSE REACTIONS

Adverse reactions associated with LEVEMIR include hypoglycemia, allergic reactions, injection site reactions, lipodystrophy, rash and pruritus (6)

To report SUSPECTED ADVERSE REACTIONS, contact Novo Nordisk Inc. at 1-800-727-6500 or FDA at 1-800-FDA-1088 or www.fda.gov/medwatch

7 DRUG INTERACTIONS

- Certain drugs may affect glucose metabolism requiring insulin dose adjustment and close monitoring of blood glucose (7)
- The signs of hypoglycemia may be reduced or absent in patients taking anti-adrenergic drugs (e.g., beta-blockers, clonidine, guanethidine, and reserpine). (7)

8 USE IN SPECIFIC POPULATIONS

Pregnancy category C: Use during pregnancy only if the potential benefit justifies the potential risk to the fetus (8.1)

Pediatric: Has not been studied in children with type 2 diabetes. Has not been studied in children with type 1 diabetes < 6 years of age (8.4)

FULL PRESCRIBING INFORMATION

1 INDICATIONS AND USAGE

LEVEMIR is indicated to improve glycemic control in adults and children with diabetes mellitus.

Important Limitations of Use:

- LEVEMIR is not recommended for the treatment of diabetic ketoacidosis. Intravenous rapid-acting or short-acting insulin is the preferred treatment for this condition.

2 DOSAGE AND ADMINISTRATION

2.1 Dosing

LEVEMIR is a recombinant human insulin analog for once- or twice-daily subcutaneous administration.

Patients treated with LEVEMIR once-daily should administer the dose with the evening meal or at bedtime.

Patients who require twice-daily dosing can administer the evening dose with the evening meal, at bedtime, or 12 hours after the morning dose.

The dose of LEVEMIR must be individualized based on clinical response. Blood glucose monitoring is essential in all patients receiving insulin therapy.

Patients adjusting the amount or timing of dosing with LEVEMIR should only do so under medical supervision with appropriate glucose monitoring [see Warnings and Precautions (5.1)].

In patients with type 1 diabetes, LEVEMIR must be used in a regimen with rapid-acting or short-acting insulin.

As with all insulins, injection sites should be rotated within the same region (abdomen, thigh, or deltoid) from one injection to the next to reduce the risk of lipodystrophy [see Adverse Reactions (6.1)].

LEVEMIR can be injected subcutaneously in the thigh, abdominal wall, or upper arm. As with all insulins, the rate of absorption, and consequently the onset and duration of action, may be affected by exercise and other variables, such as stress, intercurrent illness, or changes in co-administered medications or meal patterns.

2.2 Initiation of LEVEMIR Therapy

The recommended starting dose of LEVEMIR in patients with type 1 diabetes should be approximately one-third of the total daily insulin requirements. Rapid-acting or short-acting, pre-meal insulin should be used to satisfy the remainder of the daily insulin requirements.

The recommended starting dose of LEVEMIR in patients with type 2 diabetes who are not currently treated with insulin is 10 Units (or 0.1-0.2 Units/kg) given once daily in the evening or divided into a twice daily regimen.

LEVEMIR doses should subsequently be adjusted based on blood glucose measurements. The dosages of LEVEMIR should be individualized under the supervision of a healthcare provider.

2.3 Converting to LEVEMIR from Other Insulin Therapies

If converting from insulin glargine to LEVEMIR, the change can be done on a unit-to-unit basis.

If converting from NPH insulin, the change can be done on a unit-to-unit basis. However, some patients with type 2 diabetes may require more LEVEMIR than NPH insulin, as observed in one trial [see Clinical Studies (14)].

As with all insulins, close glucose monitoring is recommended during the transition and in the initial weeks thereafter. Doses and timing of concurrent rapid-acting or short-acting insulins or other concomitant antidiabetic treatment may need to be adjusted.

3 DOSAGE FORMS AND STRENGTHS

LEVEMIR solution for injection 100 Unit per mL is available as:

- 3 mL LEVEMIR FlexPen®
- 10 mL vial

4 CONTRAINDICATIONS

LEVEMIR is contraindicated in patients with hypersensitivity to LEVEMIR or any of its excipients. Reactions have included anaphylaxis [see Warnings and Precautions (5.4) and Adverse Reactions (6.1)]

5 WARNINGS AND PRECAUTIONS

5.1 Dosage Adjustment and Monitoring

Glucose monitoring is essential for all patients receiving insulin therapy. Changes to an insulin regimen should be made cautiously and only under medical supervision.

Changes in insulin strength, manufacturer, type, or method of administration may result in the need for a change in the insulin dose or an adjustment of concomitant anti-diabetic treatment.

As with all insulin preparations, the time course of action for LEVEMIR may vary in different individuals or at different times in the same individual and is dependent on many conditions, including the local blood supply, local temperature, and physical activity.

5.2 Administration

LEVEMIR should only be administered subcutaneously.

Do not administer LEVEMIR intravenously or intramuscularly. The intended duration of activity of LEVEMIR is dependent on injection into subcutaneous tissue. Intravenous or intramuscular administration of the usual subcutaneous dose could result in severe hypoglycemia [see Warnings and Precautions (5.3)].

Do not use LEVEMIR in insulin infusion pumps.

Do not dilute or mix LEVEMIR with any other insulin or solution. If LEVEMIR is diluted or mixed, the pharmacokinetic or pharmacodynamic profile (e.g., onset of action, time to peak effect) of LEVEMIR and the mixed insulin may be altered in an unpredictable manner.

5.3 Hypoglycemia

Hypoglycemia is the most common adverse reaction of insulin therapy, including LEVEMIR. The risk of hypoglycemia increases with intensive glycemic control. Patients must be educated to recognize and manage hypoglycemia. Severe hypoglycemia can lead to unconsciousness or convulsions and may result in temporary or permanent impairment of brain function or death. Severe hypoglycemia requiring the assistance of another person or parenteral glucose infusion, or glucagon administration has been observed in clinical trials with insulin, including trials with LEVEMIR.

The timing of hypoglycemia usually reflects the time-action profile of the administered insulin formulations. Other factors such as changes in food intake (e.g., amount of food or timing of meals), exercise, and concomitant medications may also alter the risk of hypoglycemia [see Drug Interactions (7)].

The prolonged effect of subcutaneous LEVEMIR may delay recovery from hypoglycemia.

As with all insulins, use caution in patients with hypoglycemia unawareness and in patients who may be predisposed to hypoglycemia (e.g., the pediatric population and patients who fast or have erratic food intake). The patient's ability to concentrate and react may be impaired as a result of hypoglycemia. This may present a risk in situations where these abilities are especially important, such as driving or operating other machinery.

Early warning symptoms of hypoglycemia may be different or less pronounced under certain conditions, such as longstanding diabetes, diabetic neuropathy, use of medications such as beta-blockers, or intensified glycemic control [see Drug Interactions (7)]. These situations may result in severe hypoglycemia (and, possibly, loss of consciousness) prior to the patient’s awareness of hypoglycemia.

5.4 Hypersensitivity and Allergic Reactions

Severe, life-threatening, generalized allergy, including anaphylaxis, can occur with insulin products, including LEVEMIR.

5.5 Renal Impairment

No difference was observed in the pharmacokinetics of insulin detemir between non-diabetic individuals with renal impairment and healthy volunteers. However, some studies with human insulin have shown increased circulating insulin concentrations in patients with renal impairment. Careful glucose monitoring and dose adjustments of insulin, including LEVEMIR, may be necessary in patients with renal impairment [see Clinical Pharmacology (12.3)].

5.6 Hepatic Impairment

Non-diabetic individuals with severe hepatic impairment had lower systemic exposures to insulin detemir compared to healthy volunteers. However, some studies with human insulin have shown increased circulating insulin concentrations in patients with liver impairment. Careful glucose monitoring and dose adjustments of insulin, including LEVEMIR, may be necessary in patients with hepatic impairment [see Clinical Pharmacology (12.3)].

5.7 Drug Interactions

Some medications may alter insulin requirements and subsequently increase the risk for hypoglycemia or hyperglycemia [see Drug Interactions (7)].

6 ADVERSE REACTIONS

The following adverse reactions are discussed elsewhere:

- Hypoglycemia [see Warnings and Precautions (5.3)]
- Hypersensitivity and allergic reactions [see Warnings and Precautions (5.4)]

6.1 Clinical Trial Experience

Because clinical trials are conducted under widely varying designs, the adverse reaction rates reported in one clinical trial may not be easily compared to those rates reported in another clinical trial, and may not reflect the rates actually observed in clinical practice.

The frequencies of adverse reactions (excluding hypoglycemia) reported during LEVEMIR clinical trials in patients with type 1 diabetes mellitus and type 2 diabetes mellitus are listed in Tables 1-4 below. See Tables 5 and 6 for the hypoglycemia findings.

Table 1: Adverse reactions (excluding hypoglycemia) in two pooled clinical trials of 16 weeks and 24 weeks duration in adults with type 1 diabetes (adverse reactions with incidence ≥ 5%)
 | LEVEMIR, %; (n = 767) | NPH, %; (n = 388)
Upper respiratory tract infection | 26.1 | 21.4
Headache | 22.6 | 22.7
Pharyngitis | 9.5 | 8.0
Influenza-like illness | 7.8 | 7.0
Abdominal Pain | 6.0 | 2.6

Table 2: Adverse reactions (excluding hypoglycemia) in a 26-week trial comparing insulin aspart + LEVEMIR to insulin aspart + insulin glargine in adults with type 1 diabetes (adverse reactions with incidence ≥ 5%)
 | LEVEMIR, %; (n = 161) | Glargine, %; (n = 159)
Upper respiratory tract infection | 26.7 | 32.1
Headache | 14.3 | 19.5
Back pain | 8.1 | 6.3
Influenza-like illness | 6.2 | 8.2
Gastroenteritis | 5.6 | 4.4
Bronchitis | 5.0 | 1.9

Table 3: Adverse reactions (excluding hypoglycemia) in two pooled clinical trials of 22 weeks and 24 weeks duration in adults with type 2 diabetes (adverse reactions with incidence ≥ 5%)
 | LEVEMIR, %; (n = 432) | NPH, %; (n = 437)
Upper respiratory tract infection | 12.5 | 11.2
Headache | 6.5 | 5.3

Table 4: Adverse reactions (excluding hypoglycemia) in a 26-week clinical trial of children and adolescents with type 1 diabetes (adverse reactions with incidence ≥ 5%)
 | LEVEMIR, %; (n = 232) | NPH, %; (n = 115)
Upper respiratory tract infection | 35.8 | 42.6
Headache | 31.0 | 32.2
Pharyngitis | 17.2 | 20.9
Gastroenteritis | 16.8 | 11.3
Influenza-like illness | 13.8 | 20.9
Abdominal pain | 13.4 | 13.0
Pyrexia | 10.3 | 6.1
Cough | 8.2 | 4.3
Viral infection | 7.3 | 7.8
Nausea | 6.5 | 7.0
Rhinitis | 6.5 | 3.5
Vomiting | 6.5 | 10.4

- Hypoglycemia

Hypoglycemia is the most commonly observed adverse reaction in patients using insulin, including LEVEMIR [see Warnings and Precautions (5.3)].

Tables 5 and 6 summarize the incidence of severe and non-severe hypoglycemia in the LEVEMIR clinical trials. Severe hypoglycemia was defined as an event with symptoms consistent with hypoglycemia requiring assistance of another person and associated with either a blood glucose below 50 mg/dL or prompt recovery after oral carbohydrate, intravenous glucose or glucagon administration. Non-severe hypoglycemia was defined as an asymptomatic or symptomatic plasma glucose < 56 mg/dL (<50 mg/dL in Study A and C) that was self-treated by the patient.

The rates of hypoglycemia in the LEVEMIR clinical trials (see Section 14 for a description of the study designs) were comparable between LEVEMIR-treated patients and non-LEVEMIR-treated patients (see Tables 5 and 6).

Table 5: Hypoglycemia in Patients with Type 1 Diabetes
 |  | Study A; Type 1 Diabetes; Adults; 16 weeks; In combination with; insulin aspart |  | Study B; Type 1 Diabetes; Adults; 26 weeks; In combination with; insulin aspart |  | Study C; Type 1 Diabetes; Adults; 24 weeks; In combination with; regular insulin |  | Study D; Type 1 Diabetes; Pediatrics; 26 weeks; In combination with; insulin aspart
 |  | Twice-Daily; LEVEMIR | Twice-Daily; NPH | Twice-Daily; LEVEMIR | Once-Daily Glargine | Once-Daily LEVEMIR | Once-Daily NPH | Once- or Twice Daily LEVEMIR | Once- or Twice Daily NPH
Severe hypoglycemia | Percent of patients with at least 1 event; (n/total N) | 8.7; (24/276) | 10.6; (14/132) | 5.0; (8/161) | 10.1; (16/159) | 7.5; (37/491) | 10.2; (26/256) | 15.9; (37/232) | 20.0; (23/115)
Severe hypoglycemia | Event/patient/; year | 0.52 | 0.43 | 0.13 | 0.31 | 0.35 | 0.32 | 0.91 | 0.99
Non-severe hypoglycemia | Percent of patients (n/total N) | 88.0; (243/276) | 89.4; (118/132) | 82.0; (132/161) | 77.4; (123/159) | 88.4; (434/491) | 87.9; (225/256) | 93.1; (216/232) | 95.7; (110/115)
Non-severe hypoglycemia | Event/patient/; year | 26.4 | 37.5 | 20.2 | 21.8 | 31.1 | 33.4 | 31.6 | 37.0

Table 6: Hypoglycemia in Patients with Type 2 Diabetes
 |  | Study E; Type 2 Diabetes; Adults; 24 weeks; In combination with; oral agents |  | Study F; Type 2 Diabetes; Adults; 22 weeks; In combination with; insulin aspart
 |  | Twice-Daily LEVEMIR | Twice-Daily NPH | Once- or Twice Daily LEVEMIR | Once- or Twice Daily NPH
Severe hypoglycemia | Percent of patients with at least 1 event (n/total N) | 0.4; (1/237) | 2.5; (6/238) | 1.5; (3/195) | 4.0; (8/199)
Severe hypoglycemia | Event/patient/year | 0.01 | 0.08 | 0.04 | 0.13
Non-severe hypoglycemia | Percent of patients (n/total N) | 40.5; (96/237) | 64.3; (153/238) | 32.3; (63/195) | 32.2; (64/199)
Non-severe hypoglycemia | Event/patient/year | 3.5 | 6.9 | 1.6 | 2.0

- Insulin Initiation and Intensification of Glucose Control

Intensification or rapid improvement in glucose control has been associated with a transitory, reversible ophthalmologic refraction disorder, worsening of diabetic retinopathy, and acute painful peripheral neuropathy. However, long-term glycemic control decreases the risk of diabetic retinopathy and neuropathy.

- Lipodystrophy

Long-term use of insulin, including LEVEMIR, can cause lipodystrophy at the site of repeated insulin injections. Lipodystrophy includes lipohypertrophy (thickening of adipose tissue) and lipoatrophy (thinning of adipose tissue), and may affect insulin adsorption. Rotate insulin injection sites within the same region to reduce the risk of lipodystrophy [see Dosage and Administration (2.1)].

- Weight Gain

Weight gain can occur with insulin therapy, including LEVEMIR, and has been attributed to the anabolic effects of insulin and the decrease in glucosuria.

- Peripheral Edema

Insulin, including LEVEMIR, may cause sodium retention and edema, particularly if previously poor metabolic control is improved by intensified insulin therapy.

- Allergic Reactions

Local Allergy

As with any insulin therapy, patients taking LEVEMIR may experience injection site reactions, including localized erythema, pain, pruritis, urticaria, edema, and inflammation. In clinical studies in adults, three patients treated with LEVEMIR reported injection site pain (0.25%) compared to one patient treated with NPH insulin (0.12%). The reports of pain at the injection site did not result in discontinuation of therapy.

Rotation of the injection site within a given area from one injection to the next may help to reduce or prevent these reactions. In some instances, these reactions may be related to factors other than insulin, such as irritants in a skin cleansing agent or poor injection technique. Most minor reactions to insulin usually resolve in a few days to a few weeks.

Systemic Allergy

Severe, life-threatening, generalized allergy, including anaphylaxis, generalized skin reactions, angioedema, bronchospasm, hypotension, and shock may occur with any insulin, including LEVEMIR, and may be life-threatening [see Warnings and Precautions (5.4)].

- Antibody Production

All insulin products can elicit the formation of insulin antibodies. These insulin antibodies may increase or decrease the efficacy of insulin and may require adjustment of the insulin dose. In phase 3 clinical trials of LEVEMIR, antibody development has been observed with no apparent impact on glycemic control.

6.2 Postmarketing Experience

The following adverse reactions have been identified during post approval use of LEVEMIR. Because these reactions are reported voluntarily from a population of uncertain size, it is not always possible to reliably estimate their frequency or establish a causal relationship to drug exposure.

Medication errors have been reported during post-approval use of LEVEMIR in which other insulins, particularly rapid-acting or short-acting insulins, have been accidentally administered instead of LEVEMIR [see Patient Counseling Information (17)]. To avoid medication errors between LEVEMIR and other insulins, patients should be instructed always to verify the insulin label before each injection.

7 DRUG INTERACTIONS

A number of medications affect glucose metabolism and may require insulin dose adjustment and particularly close monitoring.

The following are examples of medications that may increase the blood-glucose-lowering effect of insulins including LEVEMIR and, therefore, increase the susceptibility to hypoglycemia: oral antidiabetic medications, pramlintide acetate, angiotensin converting enzyme (ACE) inhibitors, disopyramide, fibrates, fluoxetine, monoamine oxidase (MAO) inhibitors, propoxyphene, pentoxifylline, salicylates, somatostatin analogs, and sulfonamide antibiotics.

The following are examples of medications that may reduce the blood-glucose-lowering effect of insulins including LEVEMIR: corticosteroids, niacin, danazol, diuretics, sympathomimetic agents (e.g., epinephrine, albuterol, terbutaline), glucagon, isoniazid, phenothiazine derivatives, somatropin, thyroid hormones, estrogens, progestogens (e.g., in oral contraceptives), protease inhibitors and atypical antipsychotic medications (e.g. olanzapine and clozapine).

Beta-blockers, clonidine, lithium salts, and alcohol may either increase or decrease the blood-glucose-lowering effect of insulin. Pentamidine may cause hypoglycemia, which may sometimes be followed by hyperglycemia.

The signs of hypoglycemia may be reduced or absent in patients taking anti-adrenergic drugs such as beta-blockers, clonidine, guanethidine, and reserpine.

8 USE IN SPECIFIC POPULATIONS

8.1 Pregnancy

Pregnancy Category C: In a fertility and embryonic development study, insulin detemir was administered to female rats before mating, during mating, and throughout pregnancy at doses up to 300 nmol/kg/day (3 times a human dose of 0.5 Units/kg/day, based on plasma area under the curve (AUC) ratio). Doses of 150 and 300 nmol/kg/day produced numbers of litters with visceral anomalies. Doses up to 900 nmol/kg/day (approximately 135 times a human dose of 0.5 Units/kg/day based on AUC ratio) were given to rabbits during organogenesis. Drug-dose related increases in the incidence of fetuses with gallbladder abnormalities such as small, bilobed, bifurcated, and missing gallbladders were observed at a dose of 900 nmol/kg/day. The rat and rabbit embryofetal development studies that included concurrent human insulin control groups indicated that insulin detemir and human insulin had similar effects regarding embryotoxicity and teratogenicity.

There are no well-controlled clinical studies of the use of LEVEMIR in pregnant women. Patients should be advised to discuss with their healthcare provider if they intend to, or if they become, pregnant. Because animal reproduction studies are not always predictive of human response, LEVEMIR should be used during pregnancy only if the potential benefit justifies the potential risk to the fetus. It is essential for patients with diabetes or a history of gestational diabetes to maintain good metabolic control before conception and throughout pregnancy. Insulin requirements may decrease during the first trimester, generally increase during the second and third trimesters, and rapidly decline after delivery. Careful monitoring of glucose control is essential in these patients.

8.3 Nursing Mothers

It is unknown whether LEVEMIR is excreted in human milk. Because many drugs, including human insulin, are excreted in human milk, use caution when administering LEVEMIR to a nursing woman. Use of LEVEMIR is compatible with breastfeeding, but women with diabetes who are lactating may require adjustments of their insulin doses.

8.4 Pediatric Use

The pharmacokinetics, safety and effectiveness of subcutaneous injections of LEVEMIR have been established in pediatric patients (age 6 to 17 years) with type 1 diabetes [see Clinical Pharmacology (12.3) and Clinical Studies (14)]. LEVEMIR has not been studied in pediatric patients younger than 6 years of age with type 1 diabetes. LEVEMIR has not been studied in pediatric patients with type 2 diabetes.

The dose recommendation when converting to LEVEMIR is the same as that described for adults [see Dosage and Administration (2) and Clinical Studies (14)]. As in adults, the dosage of LEVEMIR must be individualized in pediatric patients based on metabolic needs and frequent monitoring of blood glucose.

8.5 Geriatric Use

In controlled clinical trials comparing LEVEMIR to NPH insulin or insulin glargine, 64 of 1624 patients (3.9%) in the type 1 diabetes trials and 309 of 1082 patients (28.6%) in the type 2 diabetes trials were ≥65 years of age. A total of 52 (7 type 1 and 45 type 2) patients (1.9%) were ≥75 years of age. No overall differences in safety or effectiveness were observed between these patients and younger patients, but small sample sizes, particularly for patients ≥65 years of age in the type 1 diabetes trials and for patients ≥75 years of age in all trials limits conclusions. Greater sensitivity of some older individuals cannot be ruled out. In elderly patients with diabetes, the initial dosing, dose increments, and maintenance dosage should be conservative to avoid hypoglycemia. Hypoglycemia may be difficult to recognize in the elderly.

10 OVERDOSAGE

An excess of insulin relative to food intake, energy expenditure, or both may lead to severe and sometimes prolonged and life-threatening hypoglycemia. Mild episodes of hypoglycemia usually can be treated with oral glucose. Adjustments in drug dosage, meal patterns, or exercise may be needed.

More severe episodes with coma, seizure, or neurologic impairment may be treated with intramuscular/subcutaneous glucagon or concentrated intravenous glucose. After apparent clinical recovery from hypoglycemia, continued observation and additional carbohydrate intake may be necessary to avoid recurrence of hypoglycemia [see Warnings and Precautions (5.3)].

11 DESCRIPTION

LEVEMIR (insulin detemir [rDNA origin] injection) is a sterile solution of insulin detemir for use as a subcutaneous injection. Insulin detemir is a long-acting (up to 24-hour duration of action) recombinant human insulin analog. LEVEMIR is produced by a process that includes expression of recombinant DNA in Saccharomyces cerevisiae followed by chemical modification.

Insulin detemir differs from human insulin in that the amino acid threonine in position B30 has been omitted, and a C14 fatty acid chain has been attached to the amino acid B29. Insulin detemir has a molecular formula of C267H402O76N64S6 and a molecular weight of 5916.9. It has the following structure:

Figure 1: Structural Formula of insulin detemir

LEVEMIR is a clear, colorless, aqueous, neutral sterile solution. Each milliliter of LEVEMIR contains 100 units (14.2 mg/mL) insulin detemir, 65.4 mcg zinc, 2.06 mg m-cresol, 16.0 mg glycerol, 1.80 mg phenol, 0.89 mg disodium phosphate dihydrate, 1.17 mg sodium chloride, and water for injection. Hydrochloric acid and/or sodium hydroxide may be added to adjust pH. LEVEMIR has a pH of approximately 7.4.

12 CLINICAL PHARMACOLOGY

12.1 Mechanism of Action

The primary activity of insulin detemir is the regulation of glucose metabolism. Insulins, including insulin detemir, exert their specific action through binding to insulin receptors. Receptor-bound insulin lowers blood glucose by facilitating cellular uptake of glucose into skeletal muscle and adipose tissue and by inhibiting the output of glucose from the liver. Insulin inhibits lipolysis in the adipocyte, inhibits proteolysis, and enhances protein synthesis.

12.2 Pharmacodynamics

Insulin detemir is a soluble, long-acting basal human insulin analog with up to a 24-hour duration of action. The pharmacodynamic profile of LEVEMIR is relatively constant with no pronounced peak.

The duration of action of LEVEMIR is mediated by slowed systemic absorption of insulin detemir molecules from the injection site due to self-association of the drug molecules. In addition, the distribution of insulin detemir to peripheral target tissues is slowed because of binding to albumin.

Figure 2 shows results from a study in patients with type 1 diabetes conducted for a maximum of 24 hours after the subcutaneous injection of LEVEMIR or NPH insulin. The mean time between injection and the end of pharmacological effect for insulin detemir ranged from 7.6 hours to > 24 hours (24 hours was the end of the observation period).

Figure 2: Activity Profiles in Patients with Type 1 Diabetes in a 24-hour Glucose Clamp Study

For doses in the interval of 0.2 to 0.4 Units/kg, insulin detemir exerts more than 50% of its maximum effect from 3 to 4 hours up to approximately 14 hours after dose administration.

Figure 3 shows glucose infusion rate results from a 16-hour glucose clamp study in patients with type 2 diabetes. The clamp study was terminated at 16 hours according to protocol.

Figure 3: Activity Profiles in Patients with Type 2 Diabetes in a 16-hour Glucose Clamp Study

12.3 Pharmacokinetics

Absorption and Bioavailability

After subcutaneous injection of LEVEMIR in healthy subjects and in patients with diabetes, insulin detemir serum concentrations had a relatively constant concentration/time profile over 24 hours with the maximum serum concentration (Cmax) reached between 6-8 hours post-dose. Insulin detemir was more slowly absorbed after subcutaneous administration to the thigh where AUC0-5h was 30-40% lower and AUC0-inf was 10% lower than the corresponding AUCs with subcutaneous injections to the deltoid and abdominal regions.

The absolute bioavailability of insulin detemir is approximately 60%.

Distribution and Elimination

More than 98% of insulin detemir in the bloodstream is bound to albumin. The results of in vitro and in vivo protein binding studies demonstrate that there is no clinically relevant interaction between insulin detemir and fatty acids or other protein-bound drugs.

Insulin detemir has an apparent volume of distribution of approximately 0.1 L/kg. After subcutaneous administration in patients with type 1 diabetes, insulin detemir has a terminal half-life of 5 to 7 hours depending on dose.

Specific Populations

Children and Adolescents- The pharmacokinetic properties of LEVEMIR were investigated in children (6-12 years), adolescents (13-17 years), and adults with type 1 diabetes. In children, the insulin detemir plasma area under the curve (AUC) and Cmax were increased by 10% and 24%, respectively, as compared to adults. There was no difference in pharmacokinetics between adolescents and adults.

Geriatrics- In a clinical trial investigating differences in pharmacokinetics of a single subcutaneous dose of LEVEMIR in young (20 to 35 years) versus elderly (≥68 years) healthy subjects, the insulin detemir AUC was up to 35% higher among the elderly subjects due to reduced clearance. As with other insulin preparations, LEVEMIR should always be titrated according to individual requirements.

Gender- No clinically relevant differences in pharmacokinetic parameters of LEVEMIR are observed between males and females.

Race- In two clinical pharmacology studies conducted in healthy Japanese and Caucasian subjects, there were no clinically relevant differences seen in pharmacokinetic parameters. The pharmacokinetics and pharmacodynamics of LEVEMIR were investigated in a clamp study comparing patients with type 2 diabetes of Caucasian, African-American, and Latino origin. Dose-response relationships for LEVEMIR were comparable in these three populations.

Renal impairment- A single subcutaneous dose of 0.2 Units/kg (1.2 nmol/kg) of LEVEMIR was administered to healthy subjects and those with varying degrees of renal impairment (mild, moderate, severe, and hemodialysis-dependent). In this study, there were no differences in the pharmacokinetics of LEVEMIR between healthy subjects and those with renal impairment. However, some studies with human insulin have shown increased circulating levels of insulin in patients with renal impairment. Careful glucose monitoring and dose adjustments of insulin, including LEVEMIR, may be necessary in patients with renal impairment [see Warnings and Precautions (5.5)].

Hepatic impairment- A single subcutaneous dose of 0.2 Units/kg (1.2 nmol/kg) of LEVEMIR was administered to healthy subjects and those with varying degrees of hepatic impairment (mild, moderate and severe). LEVEMIR exposure as estimated by AUC decreased with increasing degrees of hepatic impairment with a corresponding increase in apparent clearance. However, some studies with human insulin have shown increased circulating levels of insulin in patients with liver impairment. Careful glucose monitoring and dose adjustments of insulin, including LEVEMIR, may be necessary in patients with hepatic impairment [see Warnings and Precautions (5.6)].

Pregnancy- The effect of pregnancy on the pharmacokinetics and pharmacodynamics of LEVEMIR has not been studied [see Use in Specific Populations (8.1)].

Smoking- The effect of smoking on the pharmacokinetics and pharmacodynamics of LEVEMIR has not been studied.

13 NONCLINICAL TOXICOLOGY

13.1 Carcinogenesis, Mutagenesis, Impairment of Fertility

Standard 2-year carcinogenicity studies in animals have not been performed. Insulin detemir tested negative for genotoxic potential in the in vitro reverse mutation study in bacteria, human peripheral blood lymphocyte chromosome aberration test, and the in vivo mouse micronucleus test.

In a fertility and embryonic development study, insulin detemir was administered to female rats before mating, during mating, and throughout pregnancy at doses up to 300 nmol/kg/day (3 times a human dose of 0.5 Units/kg/day, based on plasma AUC ratio). There were no effects on fertility in the rat.

14 CLINICAL STUDIES

The efficacy and safety of LEVEMIR given once-daily at bedtime or twice-daily (before breakfast and at bedtime, before breakfast and with the evening meal, or at 12-hour intervals) was compared to that of once-daily or twice-daily NPH insulin in open-label, randomized, parallel studies of 1155 adults with type 1 diabetes mellitus, 347 pediatric patients with type 1 diabetes mellitus, and 869 adults with type 2 diabetes mellitus. The efficacy and safety of LEVEMIR given twice-daily was compared to once-daily insulin glargine in an open-label, randomized, parallel study of 320 patients with type 1 diabetes. The evening LEVEMIR dose was titrated in all trials according to pre-defined targets for fasting blood glucose. The pre-dinner blood glucose was used to titrate the morning LEVEMIR dose in those trials that also administered LEVEMIR in the morning. In general, the reduction in glycosylated hemoglobin (HbA1c) with LEVEMIR was similar to that with NPH insulin or insulin glargine.

Type 1 Diabetes – Adult

In a 16-week open-label clinical study (Study A, n=409), adults with type 1 diabetes were randomized to treatment with either LEVEMIR at 12-hour intervals, LEVEMIR administered in the morning and bedtime or NPH insulin administered in the morning and bedtime. Insulin aspart was also administered before each meal. At 16 weeks of treatment, the combined LEVEMIR-treated patients had similar HbA1c and fasting plasma glucose (FPG) reductions compared to the NPH-treated patients (Table 7). Differences in timing of LEVEMIR administration had no effect on HbA1c, fasting plasma glucose (FPG), or body weight.

In a 26-week, open-label clinical study (Study B, n=320), adults with type 1 diabetes were randomized to twice-daily LEVEMIR (administered in the morning and bedtime) or once-daily insulin glargine (administered at bedtime). Insulin aspart was administered before each meal. LEVEMIR-treated patients had a decrease in HbA1c similar to that of insulin glargine-treated patients.

In a 24-week, non-blinded clinical study (Study C, n=749), adults with type 1 diabetes were randomized to once-daily LEVEMIR or once-daily NPH insulin, both administered at bedtime and in combination with regular human insulin before each meal. LEVEMIR and NPH insulin had a similar effect on HbA1c.

Table 7: Type 1 Diabetes Mellitus – Adult
 | Study A |  | Study B |  | Study C
Treatment duration | 16 weeks |  | 26 weeks |  | 24 weeks
Treatment in combination with | NovoLog®; (insulin aspart) |  | NovoLog®; (insulin aspart) |  | Human Soluble Insulin; (regular insulin)
 | Twice-daily; LEVEMIR | Twice-daily; NPH | Twice-daily LEVEMIR | Once-daily insulin glargine | Once-daily LEVEMIR | Once-daily NPH
Number of patients treated | 276 | 133 | 161 | 159 | 492 | 257
HbA1c (%)
Baseline HbA1c | 8.6 | 8.5 | 8.9 | 8.8 | 8.4 | 8.3
Adj. mean change from baseline | -0.8 | -0.7 | -0.6 | -0.5 | -0.1 | 0.0
LEVEMIR – NPH; 95% CI for Treatment difference | -0.2; (-0.3, -0.0) |  | -0.0; (-0.2, 0.2) |  | -0.1; (-0.3, 0.0)
Basal insulin dose (units/day)
Baseline mean | 21 | 24 | 27 | 23 | 12 | 24
Mean change from baseline | 16 | 10 | 10 | 4 | 9 | 2
Total insulin dose (units/day)
Baseline mean | 48 | 54 | 56 | 51 | 46 | 57
Mean change from baseline | 17 | 10 | 9 | 6 | 11 | 3
Fasting blood glucose (mg/dL)
Baseline mean | 209 | 220 | 153 | 150 | 213 | 206
Adj. mean change from baseline | -44 | -9 | -38 | -41 | -30 | -9
Body weight (kg)
Baseline mean | 74.6 | 75.5 | 77.5 | 75.1 | 76.5 | 76.9
Mean change from baseline | 0.2 | 0.8 | 0.5 | 1.0 | -0.3 | 0.3

Baseline values were included as covariates in an ANCOVA analysis.

Type 1 Diabetes – Pediatric

In an open-label clinical study (Study D, n=347), pediatric patients (age range 6 to 17) with type 1 diabetes were randomized to 26 weeks of treatment with LEVEMIR or NPH insulin both of which were administered either once- or twice-daily (bedtime or morning and bedtime), at a dosing frequency consistent with the number of daily basal insulin injections a patient was taking prior to trial entry. Insulin aspart was administered before each meal. LEVEMIR-treated patients had a decrease in HbA1c similar to that of NPH insulin (Table 8).

Table 8: Type 1 Diabetes Mellitus – Pediatric
 | Study D
Treatment duration | 26 weeks
Treatment in combination with | NovoLog®; (insulin aspart)
 | Once- or Twice Daily LEVEMIR | Once- or Twice Daily; NPH
Number of subjects treated | 232 | 115
HbA1c (%)
Baseline HbA1c | 8.8 | 8.8
Adj. mean change from baseline | -0.7 | -0.8
LEVEMIR – NPH; 95% CI for Treatment difference | 0.1; (-0.1, 0.3)
Basal insulin dose (units/day)
Baseline mean | 24 | 26
Mean change from baseline | 8 | 6
Total insulin dose (units/day)
Baseline mean | 48 | 50
Mean change from baseline | 9 | 7
Fasting blood glucose (mg/dL)
Baseline mean | 181 | 181
Adj. mean change from baseline | -39 | -21
Body weight (kg)
Baseline mean | 46.3 | 46.2
Mean change from baseline | 1.6 | 2.7

Type 2 Diabetes – Adult

In a 24-week, open-label, randomized, clinical study (Study E, n=476), LEVEMIR administered twice-daily (before breakfast and evening) was compared to NPH insulin administered twice-daily (before breakfast and evening) as part of a regimen of stable combination therapy with one or two of the following oral antidiabetic medications: metformin, an insulin secretagogue, or an alpha–glucosidase inhibitor. All patients were insulin-naïve at the time of randomization. LEVEMIR and NPH insulin similarly lowered HbA1c from baseline (Table 9).

In a 22-week, open-label, randomized, clinical study (Study F, n=395) in adults with type 2 diabetes, LEVEMIR and NPH insulin were given once- or twice-daily as part of a basal-bolus regimen with insulin aspart. As measured by HbA1c or FPG, LEVEMIR had efficacy similar to that of NPH insulin.

Table 9: Type 2 Diabetes Mellitus – Adult
 | Study E |  | Study F
Treatment duration | 24 weeks |  | 22 weeks
Treatment in combination with | oral agents |  | insulin aspart
 | Twice-daily; LEVEMIR | Twice-daily; NPH | Once- or Twice Daily LEVEMIR | Once- or Twice Daily; NPH
Number of subjects treated | 237 | 239 | 195 | 200
HbA1c (%)
Baseline HbA1c | 8.6 | 8.5 | 8.2 | 8.1
Adj. mean change from baseline | -2.0 | -2.1 | -0.6 | -0.6
LEVEMIR – NPH; 95% CI for Treatment difference | 0.1; (-0.0, 0.3) |  | -0.1; (-0.2, 0.1)
Basal insulin dose (units/day)
Baseline mean | 18 | 17 | 22 | 22
Mean change from baseline | 48 | 28 | 26 | 15
Total insulin dose (units/day)
Baseline mean | - | - | 22 | 22
Mean change from baseline | - | - | 57 | 42
Fasting blood glucose (mg/dL)
Baseline mean | 179 | 173 | - | -
Adj. mean change from baseline | -69 | -74 | - | -
Body weight (kg)
Baseline mean | 82.7 | 82.5 | 82.0 | 79.6
Mean change from baseline | 1.2 | 2.7 | 0.5 | 1.2

16 HOW SUPPLIED/STORAGE AND HANDLING

16.1 How Supplied

LEVEMIR is available in the following package sizes: each presentation containing 100 Units of insulin detemir per mL (U-100).

3 mL LEVEMIR FlexPen® NDC 54868-5883-0

FlexPen is for use with NovoFine® disposable needles. Each FlexPen is for use by a single patient. LEVEMIR FlexPen should never be shared between patients, even if the needle is changed.

16.2 Storage

Unused (unopened) LEVEMIR should be stored in the refrigerator between 2° and 8°C (36° to 46°F). Do not store in the freezer or directly adjacent to the refrigerator cooling element. Do not freeze. Do not use LEVEMIR if it has been frozen.

Unused (unopened) LEVEMIR can be kept until the expiration date printed on the label if it is stored in a refrigerator. Keep unused LEVEMIR in the carton so that it stays clean and protected from light.

If refrigeration is not possible, unused (unopened) LEVEMIR can be kept unrefrigerated at room temperature, below 30°C (86°F) as long as it is kept as cool as possible and away from direct heat and light. Unrefrigerated LEVEMIR should be discarded 42 days after it is first kept out of the refrigerator, even if the FlexPen or vial still contains insulin.

Vials:

After initial use, vials should be stored in a refrigerator, never in a freezer. If refrigeration is not possible, the in-use vial can be kept unrefrigerated at room temperature, below 30°C (86°F) as long as it is kept as cool as possible and away from direct heat and light. Refrigerated LEVEMIR vials should be discarded 42 days after initial use. Unrefrigerated LEVEMIR vials should be discarded 42 days after they are first kept out of the refrigerator.

LEVEMIR FlexPen:

After initial use, the LEVEMIR FlexPen must NOT be stored in a refrigerator and must NOT be stored with the needle in place. Keep the opened (in use) LEVEMIR FlexPen away from direct heat and light at room temperature, below 30°C (86°F). Unrefrigerated LEVEMIR FlexPens should be discarded 42 days after they are first kept out of the refrigerator.

The storage conditions are summarized in Table 10:

Table 10: Storage Conditions for LEVEMIR FlexPen and vial
 | Not in-use (unopened) Refrigerated | Not in-use (unopened) Room Temperature (below 30°C) | In-use (opened)
3 mL LEVEMIR FlexPen | Until expiration date | 42 days [The total time allowed at room temperature (below 30°C) is 42 days regardless of whether the product is in-use or not in-use.] | 42 days; Room Temperature (below 30°C); (Do not refrigerate)
10 mL vial | Until expiration date | 42 days | 42 days; Refrigerated or Room Temperature (below 30°C)

16.3 Preparation and Handling

Parenteral drug products should be inspected visually for particulate matter and discoloration prior to administration, whenever solution and container permit. LEVEMIR should be inspected visually prior to administration and should only be used if the solution appears clear and colorless.

Mixing and diluting: LEVEMIR must NOT be mixed or diluted with any other insulin or solution [See Warnings and Precautions (5.2)].

17 PATIENT COUNSELING INFORMATION

See FDA-Approved Patient Labeling (Patient Information and Instructions for Use)

17.1 Instructions for Patients

Patients should be informed that changes to insulin regimens must be made cautiously and only under medical supervision. Patients should be informed about the potential side effects of insulin

therapy, including hypoglycemia, weight gain, lipodystrophy (and the need to rotate injection sites within the same body region), and allergic reactions. Patients should be informed that the ability to concentrate and react may be impaired as a result of hypoglycemia. This may present a risk in situations where these abilities are especially important, such as driving or operating other machinery. Patients who have frequent hypoglycemia or reduced or absent warning signs of hypoglycemia should be advised to use caution when driving or operating machinery.

Accidental mix-ups between LEVEMIR and other insulins, particularly short-acting insulins, have been reported. To avoid medication errors between LEVEMIR and other insulins, patients should be instructed to always check the insulin label before each injection.

LEVEMIR must only be used if the solution is clear and colorless with no particles visible. Patients must be advised that LEVEMIR must NOT be diluted or mixed with any other insulin or solution.

Patients should be instructed on self-management procedures including glucose monitoring, proper injection technique, and management of hypoglycemia and hyperglycemia. Patients should be instructed on handling of special situations such as intercurrent conditions (illness, stress, or emotional disturbances), an inadequate or skipped insulin dose, inadvertent administration of an increased insulin dose, inadequate food intake, and skipped meals.

Patients with diabetes should be advised to inform their healthcare professional if they are pregnant or are contemplating pregnancy. Refer patients to the LEVEMIR "Patient Information" for additional information.

17.2 Never Share a LEVEMIR FlexPen Between Patients

Counsel patients that they should never share a LEVEMIR FlexPen with another person, even if the needle is changed. Sharing of the FlexPen between patients may pose a risk of transmission of infection.

Novo Nordisk®, Levemir®, NovoLog®, FlexPen®, and NovoFine® are registered trademarks of Novo Nordisk A/S.

LEVEMIR is covered by US Patent Nos. 5,750,497, 5,866,538, 6,011,007, 6,869,930 and other patents pending.

FlexPen is covered by US Patent Nos. 6,582,404, 6,004,297, 6,235,400 and other patents pending.

© 2005-2012 Novo Nordisk

Manufactured by:

Novo Nordisk A/S

DK-2880 Bagsvaerd, Denmark

For information about LEVEMIR contact:

Novo Nordisk Inc.

100 College Road West

Princeton, NJ 08540

1-800-727-6500

www.novonordisk-us.com

Additional barcode labeling by:
Physicians Total Care, Inc.
Tulsa, Oklahoma 74146

Patient Information

LEVEMIR® (LEV–uh-mere)

(insulin detemir [rDNA origin] injection)

solution for subcutaneous injection

Read the Patient Information that comes with LEVEMIR® before you start taking it and each time you get a refill. There may be new information. This leaflet does not take the place of talking with your healthcare provider about your diabetes or your treatment. Make sure that you know how to manage your diabetes. Ask your healthcare provider, if you have any questions about managing your diabetes.

What is LEVEMIR?

LEVEMIR is a man-made long-acting insulin, that is used to control high blood sugar in adults and children with diabetes mellitus.

It is not recommended to use LEVEMIR to treat diabetic ketoacidosis.

Who should not use LEVEMIR?

Do not take LEVEMIR if:

- you are allergic to any of the ingredients in LEVEMIR. See the end of this leaflet for a complete list of ingredients in LEVEMIR.

What should I tell my healthcare provider before taking LEVEMIR?

Before you take LEVEMIR, tell your healthcare provider if you:

- have liver or kidney problems
- have any other medical conditions. Some medical conditions can affect your insulin needs and your dose of LEVEMIR.
- are pregnant or plan to become pregnant. It is not known, if LEVEMIR would harm your unborn baby. Talk to your healthcare provider, if you are pregnant or plan to become pregnant. You and your healthcare provider should talk about the best way to manage your diabetes while you are pregnant.
- are breastfeeding or plan to breast-feed. It is not known if LEVEMIR passes into breast milk. You and your healthcare provider should decide if you will take LEVEMIR while you breastfeed.

Tell your healthcare provider about all the medicines you take, including prescription and non-prescription medicines, vitamins and herbal supplements. LEVEMIR may affect the way other medicines work, and other medicines may affect how LEVEMIR works.

Know the medicines you take. Keep a list of your medicines with you to show your healthcare provider and pharmacist when you get a new medicine.

How should I take LEVEMIR?

- Take LEVEMIR exactly as your healthcare provider told you to take it.
- Your healthcare provider will tell you how much LEVEMIR to take and when to take it.
- Do not make any changes to your dose or type of insulin unless you are told to do so by your healthcare provider.

Know your insulin. Make sure you know:

- the type and strength of insulin prescribed for you.
- the amount of insulin you take.
- the best time for you to take your insulin. This may change if you take a different type of insulin.

- Do not dilute or mix LEVEMIR with any other insulin or solution. Your LEVEMIR will not work the right way and you may lose blood sugar control, which can be serious.
- Do not use LEVEMIR in an insulin pump.
- Inject LEVEMIR under your skin (subcutaneously) in your upper arm, abdomen (stomach area), or thigh. Never inject LEVEMIR into a vein or muscle.
- Change injection sites within the area you choose with each dose. Do not inject into the exact same spot for each injection.
- Read the instructions for use that comes with your LEVEMIR. Talk to your healthcare provider if you have any questions. Your healthcare provider should show you how to inject LEVEMIR before you start taking it.
- Your healthcare provider will decide which type of LEVEMIR to prescribe for you.
  LEVEMIR comes in:
  - 10 mL vials (small bottles) for use with a syringe
  - 3 mL LEVEMIR FlexPen®

Ask your healthcare provider how you should use LEVEMIR.

- If you take too much LEVEMIR, your blood sugar may fall low (hypoglycemia). You can treat mild low blood sugar (hypoglycemia) by drinking or eating something sugary right away (fruit juice, sugar candies, or glucose tablets). It is important to treat low blood sugar (hypoglycemia) right away because it could get worse and you could pass out (lose consciousness).

If you pass out you will need help from another person or emergency medical services right away. See “What are the possible side effects of LEVEMIR?” for more information on low blood sugar (hypoglycemia).

- If you forget to take your dose of LEVEMIR, your blood sugar may go too high (hyperglycemia). If high blood sugar (hyperglycemia) is not treated it can lead to serious problems, like loss of consciousness (passing out), coma or even death.

Follow your healthcare provider’s instructions for treating high blood sugar.

Know your symptoms of high blood sugar, which may include:

-
  - increased thirst
  - frequent urination
  - drowsiness
  - loss of appetite
  - a hard time breathing
  - fruity smell on the breath
  - high amounts of sugar and ketones in your urine
  - nausea, vomiting (throwing up) or stomach pain
- Do not share needles, insulin pens or syringes with others.
- Check your blood sugar levels. Ask your healthcare provider what your blood sugars should be and when you should check your blood sugar levels.

Your insulin dosage may need to change because of:

-
  - illness
  - stress
  - other medicines you take
  - change in diet
  - change in physical activity or exercise

What should I avoid while taking LEVEMIR?

- Alcohol. Drinking alcohol may affect your blood sugar when you take LEVEMIR.
- Driving and operating machinery. You may have trouble paying attention or reacting if you have low blood sugar (hypoglycemia). Be careful when you drive a car or operate machinery. Ask your healthcare provider if it is alright for you to drive if you often have:
  - low blood sugar (hypoglycemia)
  - decreased or no warning signs of low blood sugar

What are the possible side effects of LEVEMIR?

LEVEMIR can cause serious side effects, including:

- Low blood sugar (hypoglycemia). Symptoms of low blood sugar may include:
- dizziness or lightheadedness
- shakiness
- hunger
- fast heart beat
- tingling in your hands, feet, lips or tongue
- trouble concentrating or confusion
- blurred vision
- slurred speech
- anxiety or mood changes
- headache
- sweating

Very low blood sugar (hypoglycemia) can cause loss of consciousness (passing out), seizures, and death. Talk to your healthcare provider about how to tell if you have low blood sugar and what to do if this happens while taking LEVEMIR. Know your symptoms of low blood sugar. Follow your healthcare provider’s instructions for treating low blood sugar.

Talk to your healthcare provider if low blood sugar is a problem for you. Your dose of LEVEMIR may need to be changed.

- Skin thickening or pits at the injection site (lipodystrophy). Change (rotate) the area where you inject your insulin to help prevent these skin changes from happening. Do not inject insulin into areas of skin that have thickening or pits.
- Serious allergic reactions. LEVEMIR can cause life threatening symptoms. Get medical help right away if you have any of these symptoms of an allergic reaction:

- a rash all over your body
- itching
- shortness of breath
- trouble breathing (wheezing)
- fast heartbeat
- sweating
- feel faint

Common side effects of LEVEMIR include:

- Low blood sugar (hypoglycemia). See “What are the possible side effects of LEVEMIR?” for more information on low blood sugar (hypoglycemia).
- Reactions at the injection site (local allergic reaction). You may get redness, swelling, and itching at the injection site. If you keep having skin reactions or they are serious, talk to your healthcare provider.
- Weight gain. This can occur with any insulin therapy. Talk to your healthcare provider about how LEVEMIR can affect your weight.

Tell your healthcare provider if you have any side effect that bothers you or does not go away.

These are not all of the possible side effects from LEVEMIR. Ask your healthcare provider or pharmacist for more information.

Call your doctor for medical advice about side effects.

You may report side effects to FDA at 1-800-FDA-1088.

How should I store LEVEMIR?

Unopened LEVEMIR:

- Keep all unopened LEVEMIR in the refrigerator between 36°F to 46°F (2°C to 8°C).
- Unopened LEVEMIR can be kept until the expiration date on the label if the medicine has been stored in a refrigerator.
- If refrigeration is not possible, you can keep the unopened LEVEMIR at room temperature below 86°F (30°C).
- Throw away LEVEMIR 42 days after it is first kept out of the refrigerator.
- Do not freeze. Do not use LEVEMIR if it has been frozen.
- Keep unopened LEVEMIR in the carton to protect it from light.

LEVEMIR in use:

- Vials
  - Keep opened vials of LEVEMIR in the refrigerator or at room temperature below 86°F (30°C) away from direct heat or light.
  - Throw away a vial that has always been kept in the refrigerator after 42 days of use, even if there is insulin left in the vial.
  - Throw away a vial that has been kept at room temperature 42 days after it is first kept out of the refrigerator, even if there is insulin left in the vial.

- LEVEMIR FlexPen
  - Keep at room temperature below 86°F (30°C) for up to 42 days.
  - Do not store a LEVEMIR FlexPen that you are using in the refrigerator.
  - Do not store LEVEMIR with the needle attached.
  - Keep LEVEMIR FlexPen away from direct heat or light.
  - Throw away used LEVEMIR FlexPens after 42 days, even if there is insulin left in them.

Keep LEVEMIR and all medicines out of the reach of children.

General information about LEVEMIR

Medicines are sometimes prescribed for conditions that are not mentioned in the patient leaflet. Do not use LEVEMIR for a condition for which it was not prescribed. Do not give LEVEMIR to other people, even if they have the same symptoms you have. It may harm them.

This leaflet summarizes the most important information about LEVEMIR. If you would like more information about LEVEMIR or diabetes, talk with your healthcare provider. You can ask your healthcare provider for information about LEVEMIR that is written for healthcare professionals.

For more information about LEVEMIR, call 1-800-727-6500 or go to www.novonordisk-us.com.

What are the ingredients in LEVEMIR?

Active Ingredient: Insulin detemir

Inactive Ingredients: zinc, m-cresol, glycerol, phenol, disodium phosphate dehydrate, sodium chloride and water for injection. Hydrochloric acid or sodium hydroxide may be added.

This Patient Information has been approved by the U.S. Food and Drug Administration.

Revised: January 2012

Novo Nordisk®, LEVEMIR®, and FlexPen® are registered trademarks of Novo Nordisk A/S.

LEVEMIR® is covered by US Patent Nos. 5,750,497, 5,866,538, 6,011,007, 6,869,930 and other patents pending.

FlexPen® is covered by US Patent Nos. 6,582,404, 6,004,297, 6,235,004 and other patents pending.

© 2005-2012 Novo Nordisk

Manufactured by:

Novo Nordisk A/S

DK-2880 Bagsvaerd, Denmark

For information about LEVEMIR® contact:

Novo Nordisk Inc.

100 College Road West

Princeton, New Jersey 08540

www.novonordisk-us.com

1-800-727-6500

Patient Instructions For Use

LEVEMIR® 10 mL vial

Please read the following Instructions for use carefully before using your LEVEMIR® 10 mL vial and each time you get a refill. You should read the instructions in this manual even if you have used an insulin 10 mL vial before.

How should I use the LEVEMIR 10 mL vial?

Using the 10 mL vial:

1. Check to make sure that you have the correct type of insulin. This is especially important if you use different types of insulin.

2. Look at the vial and the insulin. The LEVEMIR insulin should be clear and colorless. The tamper-resistant cap should be in place before the first use. If the cap has been removed before your first use of the vial, or if the insulin is cloudy or colored, Do not use the insulin and return it to your pharmacy.

3. Wash your hands with soap and water.

4. If you are using a new vial, pull off the tamper-resistant cap.

Before each use, wipe the rubber stopper with an alcohol wipe.

5. Do not roll or shake the vial. Shaking the vial right before the dose is drawn into the syringe may cause bubbles or foam. This can cause you to draw up the wrong dose of insulin. The insulin should be used only if it is clear and colorless.

6. Pull back the plunger on your syringe until the black tip reaches the marking for the number of units you will inject.

7. Push the needle through the rubber stopper into the vial.

8. Push the plunger all the way in. This inserts air into the vial.

9. Turn the vial and syringe upside down and slowly pull the plunger back to a few units beyond the correct dose that you need.

10. If there are air bubbles, tap the syringe gently with your finger to raise the air bubbles to the top of the needle. Then slowly push the plunger to the correct unit marking for your dose.

11. Check to make sure you have the right dose of LEVEMIR in the syringe.

12. Pull the syringe out of the vial

13. Inject your LEVEMIR right away as instructed by your healthcare provider.

How should I inject LEVEMIR with a syringe?

If you clean your injection site with an alcohol swab, let the injection site dry before you inject. Talk with your healthcare provider about how to rotate injection sites and how to give an injection.

1. Pinch your skin between two fingers, push the needle into the skinfold, using a dart-like motion and push the plunger to inject the insulin under your skin. The needle will be straight in.

2. Keep the needle under your skin for at least 6 seconds to make sure you have injected all the insulin. After you pull the needle from your skin you may see a drop of Levemir at the needle tip. This is normal and has no effect on the dose you just received.

3. If blood appears after you pull the needle from your skin, press the injection site lightly with an alcohol swab. Do not rub the area.

4. After each injection, remove the needlewithout recapping and dispose of it in a puncture-resistant container. Used syringes, needles, and lancets should be placed in sharps containers (such as red biohazard containers), hard plastic containers (such as detergent bottles), or metal containers (such as an empty coffee can). Such containers should be sealed and disposed of properly.

Revised: January 2012

Novo Nordisk® and LEVEMIR® are registered trademarks of Novo Nordisk A/S.

LEVEMIR® is covered by US Patent Nos. 5,750,497, 5,866,538, 6,011,007, 6,869,930, and other patents pending.

© 2005-2012 Novo Nordisk

Manufactured by:

Novo Nordisk A/S

DK-2880 Bagsvaerd, Denmark

For information about LEVEMIR® contact:

Novo Nordisk Inc.

100 College Road West,

Princeton, New Jersey 08540

Instructions For Use

LEVEMIR® FlexPen®

Please carefully read the following Instructions for use before using your LEVEMIR® FlexPen® and each time you get a refill. You should read the instructions in this manual even if you have used a LEVEMIR FlexPen before.

LEVEMIR FlexPen is a disposable dial-a-dose insulin pen. You can select doses from 1 to 60 units in increments of 1 unit. LEVEMIR FlexPen is designed to be used with NovoFine® needles.

Δ LEVEMIR FlexPen should not be used by people who are blind or have severe eyesight problems without the help of a person who has good eyesight and who is trained to use the LEVEMIR FlexPen the right way.

Getting ready

Make sure you have the following items:

- LEVEMIR FlexPen
- NovoFine disposable needles
- Alcohol swab

PREPARING YOUR LEVEMIR FLEXPEN

Wash your hands with soap and water. Before you start to prepare your injection, check the label to make sure that you are taking the right type of insulin. This is especially important if you take more than 1 type of insulin. LEVEMIR should look clear and colorless.

A. Pull off the pen cap (see diagram A).

Wipe the rubber stopper with an alcohol swab.

B. Attaching the needle

Remove the protective tab from a new disposable needle.

Attach the needle tightly onto your FlexPen. It is important that the needle is put on straight (see diagram B).

Never place a disposable needle on your LEVEMIR FlexPen until you are ready to give your injection.

C. Pull off the big outer needle cap (see diagram C).

D. Pull off the inner needle cap and throw it away (see diagram D).

Δ Always use a new needle for each injection to cut down the chance of infection and to prevent blocked needles.
Δ Be careful not to bend or damage the needle before use.
Δ To reduce the risk of needle sticks, never put the inner needle cap back on the needle.

Giving the airshot before each injection

Before each injection, small amounts of air may collect in the cartridge during normal use. To avoid injecting air and to ensure you take the right dose of insulin:

E. Turn the dose selector to select 2 units (see diagram E).

F. Hold your LEVEMIR FlexPen with the needle pointing up. Tap the cartridge gently with your finger a few times to make any air bubbles collect at the top of the cartridge (see diagram F).

G. While you keep the needle pointing upwards, press the push-button all the way in (see diagram G). The dose selector returns to 0.

A drop of insulin should appear at the needle tip. If not, change the needle and repeat the procedure no more than 6 times.

If you do not see a drop of insulin after 6 times, do not use the LEVEMIR FlexPen and contact Novo Nordisk at 1-800-727-6500.

A small air bubble may remain at the needle tip, but it will not be injected.

SELECTING YOUR DOSE

Check and make sure that the dose selector is set at 0.

H. Turn the dose selector to the number of units you need to inject. The pointer should line up with your dose.

The dose can be corrected either up or down by turning the dose selector in either direction until the correct dose lines up with the pointer (see diagram H). When turning the dose selector, be careful not to press the push-button as insulin will come out.

You cannot select a dose larger than the number of units left in the cartridge.

You will hear a click for every single unit dialed. Do not set the dose by counting the number of clicks you hear.

Δ Do not use the cartridge scale printed on the cartridge to measure your dose of insulin.

GIVING THE INJECTION

Do the injection exactly as shown to you by your healthcare provider. Your healthcare provider should tell you if you need to pinch the skin before injecting. Wipe the skin with an alcohol swab and let the area dry.

I. Insert the needle into your skin.

Inject the dose by pressing the push-button all the way in until the 0 lines up with the pointer (see diagram I). Be careful only to push the button after the needle is in the skin.

Turning the dose selector will not inject insulin.

J. Keep the needle in the skin for at least 6 seconds, and keep the push-button pressed all the way in until the needle has been pulled out from the skin (see diagram J). This will make sure that the full dose has been given.

You may see a drop of LEVEMIR at the needle tip. This is normal and has no effect on the dose you just received. If blood appears after you take the needle out of your skin, press the injection site lightly with an alcohol swab. Do not rub the area.

After the injection

Carefully remove the needle from the pen after each injection. This helps to prevent infection and leakage of insulin. You can carefully recap the needle with the bigger outer cap to help make it easier to remove the needle.

Δ Do not recap the needle with the small inner cap. Recapping with this small part can increase your chances of having a needle stick injury.
Δ Put the needle in a sharps container or some type of hard plastic or metal container with a screw top such as a detergent bottle or empty coffee can. These containers should be sealed and thrown away the right way. Check with your healthcare provider about the right way to throw away used syringes and needles. There may be local or state laws about how to throw away used needles and syringes. Do not throw away used needles and syringes in household trash or recycling bins.

K. Put the pen cap on the LEVEMIR FlexPen and store the LEVEMIR FlexPen without the needle attached (see diagram K).

The LEVEMIR FlexPen prevents the cartridge from being completely emptied. It can deliver 300 units then you should throw it away in a sharps container or some type of hard plastic or metal container with a screw top, such as a detergent bottle or empty coffee can.

FUNCTION CHECK

L. If your LEVEMIR FlexPen is not working the right way, follow the steps below:

- Attach a new NovoFine needle.
- Remove the big outer needle cap and the inner needle cap.
- Do an airshot as described in “Giving the airshot before each injection” (see diagram E through G).
- Put the big outer needle cap onto the needle. Do not put on the inner needle cap.
- Turn the dose selector so the dose indicator window shows 20 units.
- Hold the LEVEMIR FlexPen so the needle is pointing down.
- Press the push-button all the way in.

The insulin should fill the lower part of the big outer needle cap to the marker (see diagram L). If LEVEMIR FlexPen has released too much or too little insulin, do the function check again. If the same problem happens again, do not use your LEVEMIR FlexPen and contact Novo Nordisk at 1-800-727-6500.

Maintenance

Your FlexPen is designed to work accurately and safely. It must be handled with care. If you drop your FlexPen it could get damaged. If you are concerned that your FlexPen is damaged, use a new one. You can clean the outside of your FlexPen by wiping it with a damp cloth. Do not soak or wash your FlexPen. Soaking or washing the FlexPen could damage it. Do not refill your FlexPen.

Δ Remove the needle from the LEVEMIR FlexPen after each injection. This helps to cut down your chance of infection, prevent leakage of insulin. Be careful when handling used needles to avoid needle sticks and transfer of infections.
Δ Keep your LEVEMIR FlexPen and needles out of the reach of children.
Δ Use LEVEMIR FlexPen as directed to treat your diabetes. Needles and LEVEMIR FlexPen must not be shared.
Δ Always use a new needle for each injection.
Δ Novo Nordisk is not responsible for harm due to using this insulin pen with products not recommended by Novo Nordisk.
Δ As a safety measure, always carry a spare insulin delivery device in case your LEVEMIR FlexPen is lost or damaged.
Δ Remember to keep the disposable LEVEMIR FlexPen with you. Do not leave it in a car or other location where it can get too hot or too cold.

Revised: January 2012

Novo Nordisk® , LEVEMIR® , FlexPen® , NovoPen® , and NovoFine® are registered trademarks of Novo Nordisk A/S.

LEVEMIR® is covered by US Patent Nos. 5,750,497, 5,866,538, 6,011,007, 6,869,930, and other patents pending.

FlexPen® is covered by US Patent Nos. 6,582,404, 6,004,297, 6,235,004, and other patents pending.

© 2005-2012 Novo Nordisk

Manufactured by:

Novo Nordisk A/S

DK-2880 Bagsvaerd, Denmark

For information about LEVEMIR® contact:

Novo Nordisk Inc.

100 College Road West,

Princeton, New Jersey 08540

Package Label - Principal Display Panel - 3 mL FlexPen

NDC 54868-5883-0

List 643910

Levemir® FlexPen®

Insulin detemir (rDNA origin) injection

100 units/mL (U-100)

5x3 mL Prefilled Pens

For subcutaneous use only

Rx Only

Single Patient use only

For use with NovoFine® disposable needles.

Keep in a cold place.

Store at 2° - 8°C (36° - 46°F).

Avoid freezing.

Protect from light.